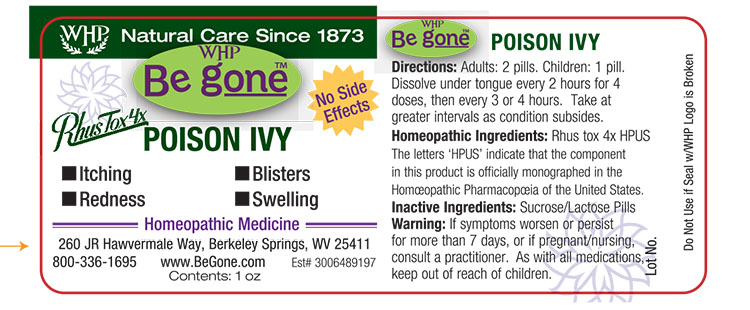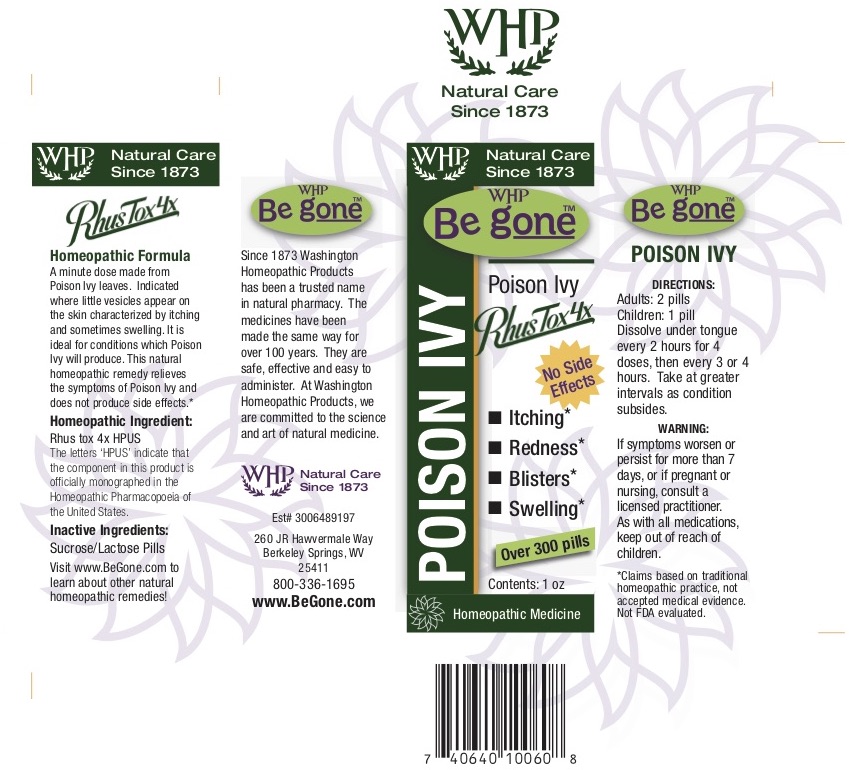 DRUG LABEL: Be gone Poison Ivy

NDC: 68428-725 | Form: PELLET
Manufacturer: Washington Homeopathic Products
Category: homeopathic | Type: HUMAN OTC DRUG LABEL
Date: 20190619

ACTIVE INGREDIENTS: TOXICODENDRON PUBESCENS LEAF 4 [hp_X]/1 1
INACTIVE INGREDIENTS: SUCROSE; LACTOSE

DRUG FACTS

ACTIVE INGREDIENTS

RHUS TOX 4X

USES

To relieve the symptoms of conditions produced by Poison Oak and Poison Ivy

KEEP OUT OF REACH OF CHILDREN

As with all medications, keep out of reach of children.

INDICATIONS

RHUS TOX Better motion

STOP USE AND ASK DOCTOR

If symptoms persist or recur, discontinue use. If pregnant or nursing, consult a licensed practitioner before using this product.

DIRECTIONS

Adults 2 pills. Children: 1 pellet. Disolve on tongue every two hours for four doses. Then every three or four hours. Take at greater intervals as condition subsides.

INACTIVE INGREDIENTS

Sucrose/Lactose

PRINCIPAL DISPLAY PANEL

Be g oneTM Poison Ivy label

Be g oneTM Poison Ivy box

*Claims based on traditional homeopathic practice, not accepted medical evidence. Not FDA evaluated.